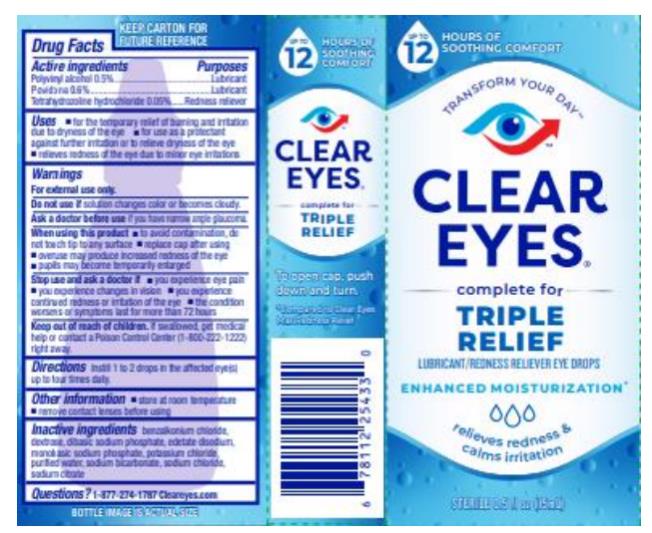 DRUG LABEL: Clear Eyes Triple Relief
NDC: 67172-898 | Form: LIQUID
Manufacturer: Prestige Brands Holdings, Inc.
Category: otc | Type: HUMAN OTC DRUG LABEL
Date: 20241025

ACTIVE INGREDIENTS: POLYVINYL ALCOHOL, UNSPECIFIED 5 mg/1 mL; POVIDONE 6 mg/1 mL; TETRAHYDROZOLINE HYDROCHLORIDE 0.5 mg/1 mL
INACTIVE INGREDIENTS: BENZALKONIUM CHLORIDE; DEXTROSE; SODIUM PHOSPHATE, DIBASIC; EDETATE DISODIUM; SODIUM PHOSPHATE, MONOBASIC; POTASSIUM CHLORIDE; WATER; SODIUM BICARBONATE; SODIUM CHLORIDE; SODIUM CITRATE

Clear Eyes Triple Relief

Drug Facts

Active ingredients

Polyvinyl alcohol 0.5%

Purpose

Lubricant

Active ingredients

Povidone 0.6%

Purpose

Lubricant

Active ingredient

Tetrahydrozoline hydrochloride 0.05%

Purpose

Redness reliever

Uses

- for the temporary relief of burning & irritation due to dryness of the eye
- for use as a protectant against further irritation or to relieve dryness of the eye
- relieves redness of the eye due to minor eye irritations

Warnings

For external use only.

Do not use if

solution changes color or becomes cloudy.

Ask a doctor before use if you have

narrow angle glaucoma.

When using this product

- to avoid contamination, do not touch tip to any surface
- replace cap after using
- overuse may produce increased redness of the eye
- pupils may become temporarily enlarged

Stop use & ask a doctor if

- you experience eye pain
- you experience changes in vision
- you experience continued redness or irritation of the eye
- the condition worsens or symptoms last for more than 72 hours

Keep out of reach of children.

If swallowed, get medical help or contact a Poison Control Center (1-800-222-1222) right away.

Directions

Instill 1 to 2 drops in the affected eye(s) up to four times daily.

Other information

- store at room temperature
- remove contact lenses before using

Inactive ingredients

benzalkonium chloride, dextrose, dibasic sodium phosphate, edetate disodium, monobasic sodium phosphate, potassium chloride, purified water, sodium bicarbonate, sodium chloride, sodium citrate

Questions?

1-877-274-1787 Cleareyes.com

PRINCIPAL DISPLAY PANEL

CLEAR EYES®
TRIPLE RELIEF
LUBRICANT/REDNESS RELIEVER EYE DROPS
STERILE 0.5 FL OZ (15 mL)